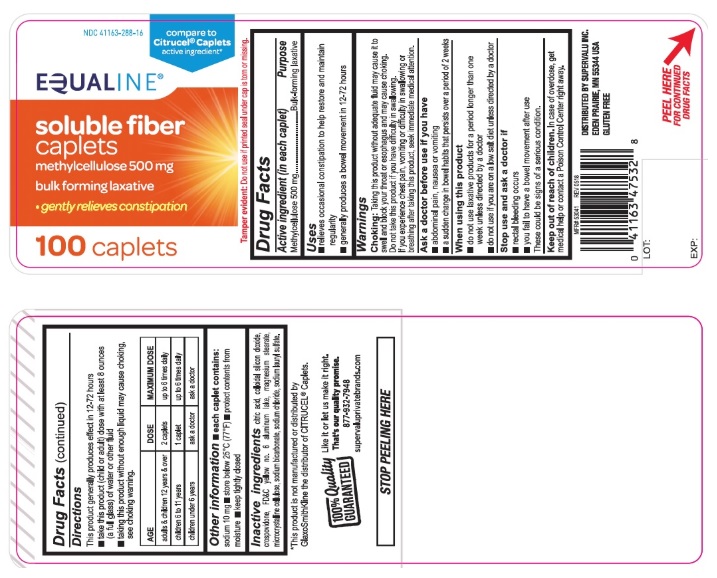 DRUG LABEL: Soluble Fiber
NDC: 41163-288 | Form: TABLET
Manufacturer: United Natural Foods, Inc. dba UNFI
Category: otc | Type: Human OTC Drug Label
Date: 20250120

ACTIVE INGREDIENTS: METHYLCELLULOSE (4000 CPS) 500 mg/1 1
INACTIVE INGREDIENTS: ANHYDROUS CITRIC ACID; SILICON DIOXIDE; CROSPOVIDONE, UNSPECIFIED; FD&C YELLOW NO. 6; MAGNESIUM STEARATE; CELLULOSE, MICROCRYSTALLINE; SODIUM BICARBONATE; SODIUM LAURYL SULFATE; SODIUM CHLORIDE

Equaline soluble fiber caplets

ACTIVE INGREDIENT (in each caplet)

Methylcellulose 500 mg

PURPOSE

Bulk-forming laxative

USE(S)

- relieves occasional constipation to help restore and maintain regularity
- generally produces a bowel movement in 12-72 hours

WARNINGS

Choking: Taking this product without adequate fluid may cause it to swell and block your throat or esophagus and may cause choking. Do not take this product if you have difficulty in swallowing. If you experience chest pain, vomiting or difficulty in swallowing or breathing after taking this product, seek immediate medical attention.

ASK A DOCTOR BEFORE USE IF YOU HAVE

- abdominal pain, nausea or vomiting
- a sudden change in bowel habits that persists over a period of 2 weeks

WHEN USING THIS PRODUCT

- do not use laxative products for a period longer than one week unless directed by a doctor.
- do not use if you are on a low salt diet unless directed by a doctor.

STOP USE AND ASK DOCTOR IF

- rectal bleeding occurs
- you fail to have a bowel movement after use

These could be signs of a serious condition

KEEP OUT OF REACH OF CHILDREN

In case of overdose, get medical help or contact a Poison Control Center right away

DOSAGE & ADMINISTRATION SECTION

Directions

This product generally produces effect in 12-72 hours

- take this product (child or adult) dose with atleast 8 ounces (a full glass) of water or other fluid
- taking this product without enough liquid may cause choking, see choking warning.

AGE | DOSE | MAXIMUM DOSE
adults & children 12 years & over | 2 caplets | up to 6 times daily
children 6 to 11 years | 1 caplet | up to 6 times daily
children under 6 years | ask a doctor | ask a doctor

OTHER INFORMATION

- each caplet contains: sodium 10 mg
- store below 25oC (77oF)
- protect contents from moisture
- keep tightly closed

INACTIVE INGREDIENTS

citric acid, colloidal silicon dioxide, crospovidone, FD&C yellow no.6 aluminum lake, magnesium stearate, microcrystalline cellulose, sodium bicarbonate, sodium chloride, sodium lauryl sulfate.

PRINCIPAL DISPLAY PANEL

NDC 41163-288-16
Compare to Citrucel Caplets active ingredient*
EQUALINE
soluble fiber caplets
methylcellulose 500 mg
bulk forming laxative

- gently relieves constipation

100 Caplets